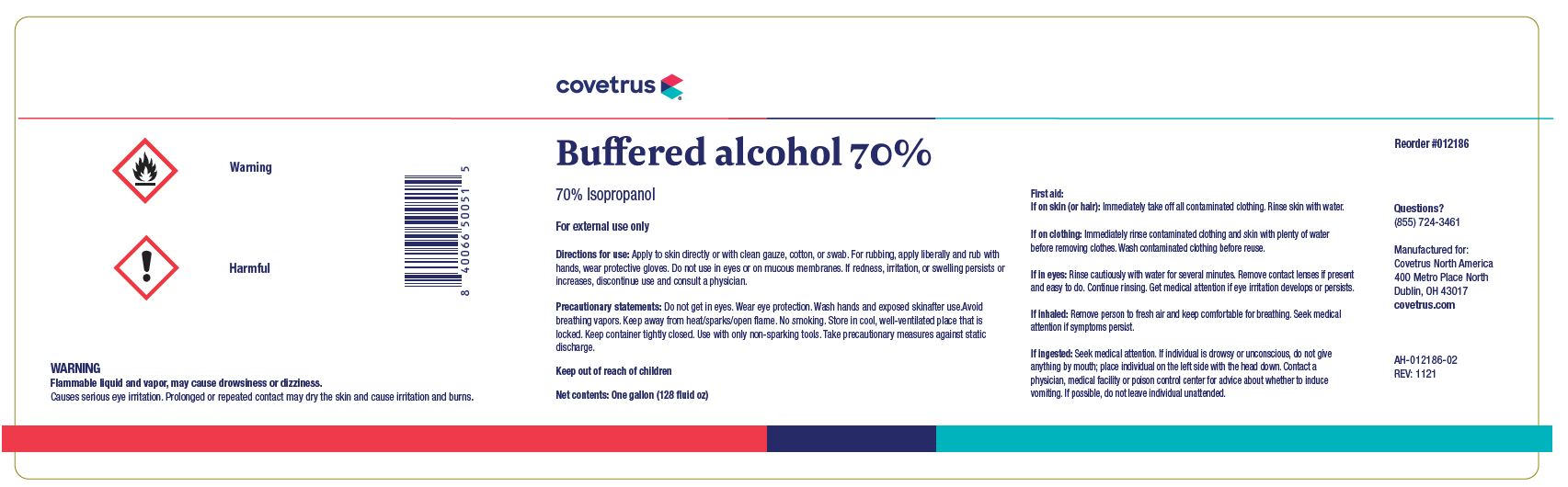 DRUG LABEL: BUFFERED ALCOHOL
NDC: 11695-5575 | Form: LIQUID
Manufacturer: Butler Animal Health Supply LLC, dba Covetrus North America
Category: animal | Type: OTC ANIMAL DRUG LABEL
Date: 20251231

ACTIVE INGREDIENTS: ISOPROPYL ALCOHOL 70 mL/100 mL

FOR EXTERNAL USE ONLY

DIRECTIONS FOR USE:

Apply to skin directly or with clean gauze, cotton or swab.

For rubbing, apply liberally and rub with hands, wear protective gloves. Do not use in eyes or on mucous membranes. If redness, irritation or swelling persists or increases, discontinue use and consult a physician.

PRECAUTIONARY STATEMENTS:

Do not get in eyes. Wear eye protection. Wash hands and exposed skin after use. Avoid breathing vapors. Keep away from heat/sparks/open flame. No smoking. Store in cool, well ventilated place that is locked. Keep container tightly closed. Use only non-sparking tools. Take precautionary measure against static discharge.

FIRST AID:

IF ON SKIN (or hair): Take off immediately all contaminated clothing. Rinse skin with water.

IF ON CLOTHING: Immediately contaminated clothing and skin with plenty of water before removing clothes. Wash contaminated clothing before reuse.

IF IN EYES: Rinse cautiously with water for several minutes. Remove contact lenses if present and easy to do. Continue rinsing. Get medical attention if eye irritation develops or persists.

IF INHALED: Remove person to fresh air and keep comfortable for breathing. Seek medical attention if symptoms persist.

IF INGESTED: Seek medical attention. If individual is drowsy or unconscious, do not give anything by mouth; place individual on the left side with the head down. Contact a physician, medical facility, or poison control center for advice about whether to induce vomiting. If possible, do not leave individual unattended.

REORDER NO. 012186

Principal Display Panel

FLAMMABLE LIQUID AND VAPOR, MAY CAUSE DROWSINESS OR DIZZINESS.

Causes serious eye irritation. Prolonged or repeated contact may dry the skin and cause

irritation and burns.